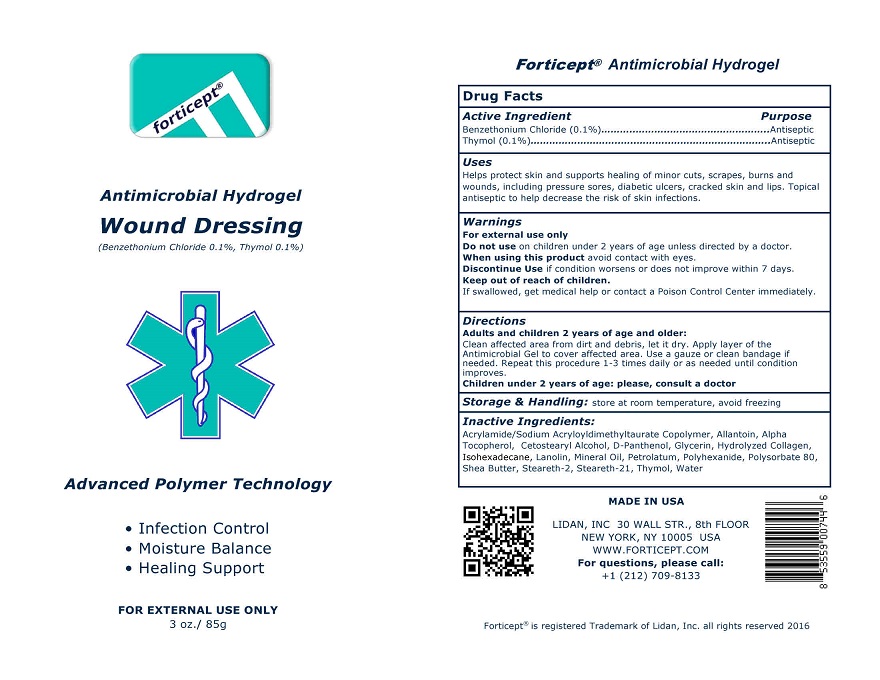 DRUG LABEL: Forticept Antimicrobial Hydrogel Wound Dressing
NDC: 72127-0901 | Form: Gel
Manufacturer: Lidan, Inc
Category: otc | Type: HUMAN OTC DRUG LABEL
Date: 20250325

ACTIVE INGREDIENTS: benzethonium chloride 1 g/1000 g; thymol 1 g/1000 g
INACTIVE INGREDIENTS: SODIUM ACRYLATE/SODIUM ACRYLOYLDIMETHYLTAURATE COPOLYMER (4000000 MW); ALLANTOIN; .ALPHA.-TOCOPHEROL ACETATE, DL-; CETOSTEARYL ALCOHOL; DEXPANTHENOL; GLYCERIN; HYDROLYSED BOVINE COLLAGEN (ENZYMATIC; 2000-5000 MW); ISOHEXADECANE; LANOLIN; MINERAL OIL; PETROLATUM; POLIHEXANIDE; POLYSORBATE 80; SHEA BUTTER; STEARETH-2; STEARETH-21; WATER

Forticept Antimicrobial Hydrogel Wound Dressing

Active Ingredient/Purpose

Benzethonium Chloride - 0.1%............Antiseptic

Thymol - 0.1%..................................Antiseptic

Uses

Helps protect skin and supports healing of minor cuts, scrapes, burns and wounds, including pressure sores, diabetic ulcers, cracked skin and lips. Topical antiseptic to help decrease the risk of skin infections.

Warnings For external use only.

Do not use on children under 2 years of age unless directed by a doctor.

When using this product avoid contact with eyes.

Stop use and ask a doctor if condition worsens, symptoms last more than 7 days or clear up and occur again within a few days.

Keep out of reach of children. If swallowed, get medical help or contact a Poison Control Center right away

Directions:

Adults and children 2 years of age and older:

Clean affected area from dirt and debris, let it dry. Apply a thin layer of Forticept Antimicrobial Gel and cover affected area with a clean bandage if needed. Repeat this procedure 1-3 times daily or as needed until condition improves.

Children under 2 years of age: please, consult a doctor

Storage and handling:

Store at room temperature, avoid freezing

Inactive ingredients:

Acrylamide/Sodium Acryloyldimethyltaurate Copolymer, Allantoin, Alpha Tocopherol, Cetostearyl Alcohol, Panthenol, Glycerin, Hydrolyzed Collagen, Isohexadecane, Lanolin, Mineral Oil, Petrolatum, Polihexanide, Polysorbate 80, Shea Butter, Steareth-2, Steareth-21, Water